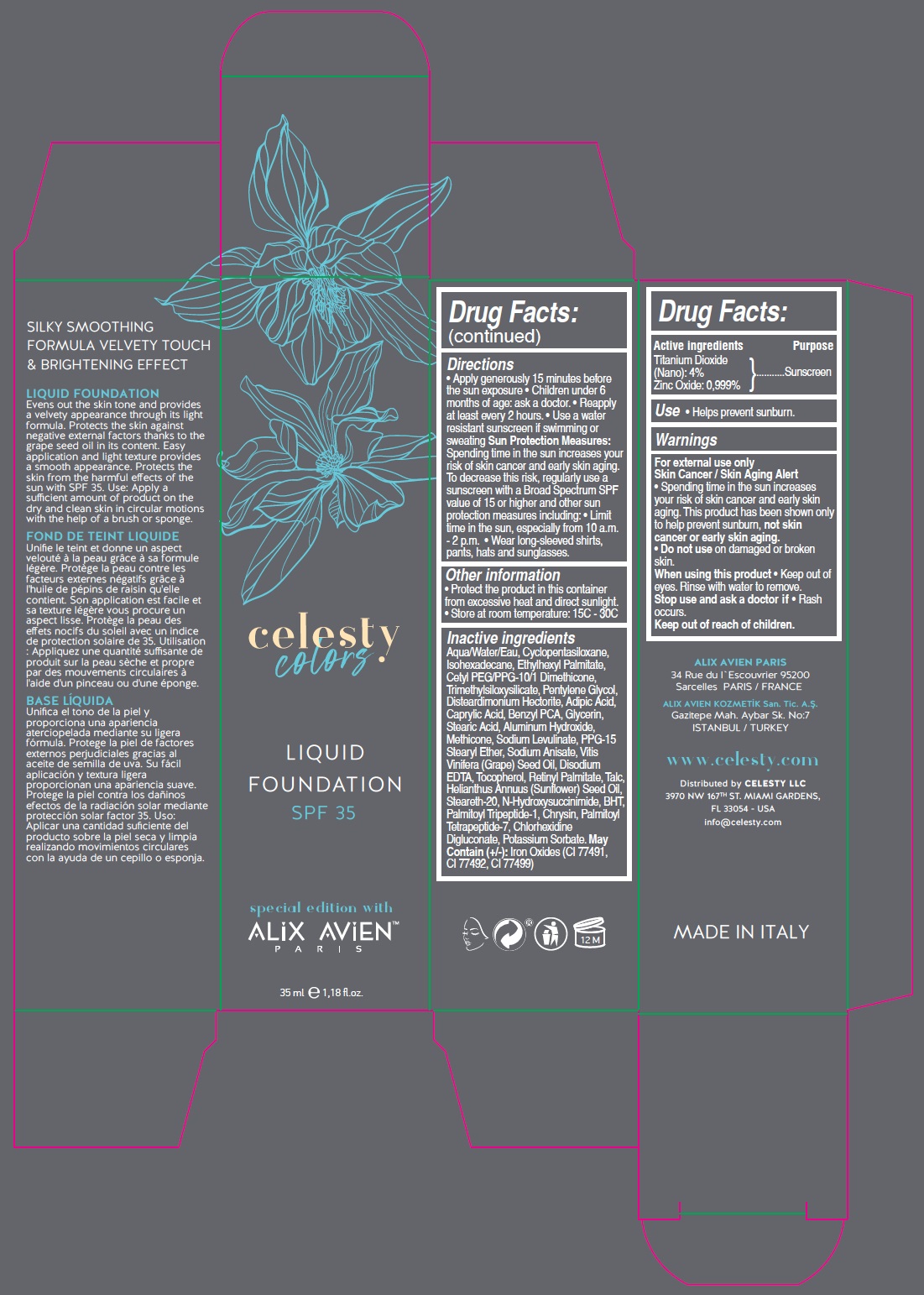 DRUG LABEL: celesty colors special edition with ALIX AVIEN
NDC: 81120-113 | Form: LIQUID
Manufacturer: MABA KOZMETIK LIMITED SIRKETI
Category: otc | Type: HUMAN OTC DRUG LABEL
Date: 20210322

ACTIVE INGREDIENTS: TITANIUM DIOXIDE 40 mg/1 mL; ZINC OXIDE 9.99 mg/1 mL
INACTIVE INGREDIENTS: WATER; CYCLOMETHICONE 5; ISOHEXADECANE; ETHYLHEXYL PALMITATE; CETYL PEG/PPG-10/1 DIMETHICONE (HLB 2); TRIMETHYLSILOXYSILICATE (M/Q 0.6-0.8); PENTYLENE GLYCOL; DISTEARDIMONIUM HECTORITE; ADIPIC ACID; CAPRYLIC ACID; BENZYL PCA; GLYCERIN; STEARIC ACID; ALUMINUM HYDROXIDE; METHICONE (20 CST); SODIUM LEVULINATE; PPG-15 STEARYL ETHER; SODIUM ANISATE; GRAPE SEED OIL; EDETATE DISODIUM ANHYDROUS; TOCOPHEROL; VITAMIN A PALMITATE; TALC; SUNFLOWER OIL; STEARETH-20; N-HYDROXYSUCCINIMIDE; BUTYLATED HYDROXYTOLUENE; PALMITOYL TRIPEPTIDE-1; CHRYSIN; PALMITOYL TETRAPEPTIDE-7; CHLORHEXIDINE GLUCONATE; POTASSIUM SORBATE; FERRIC OXIDE RED; FERRIC OXIDE YELLOW; FERROSOFERRIC OXIDE

celesty colors special edition with ALIX AVIENTM LIQUID FOUNDATION SPF 35

Active ingredients

Titanium Dioxide (Nano): 4%

Zinc Oxide: 0.999%

Purpose

Sunscreen

Use

• Helps prevent sunburn.

Warnings

For external use only

Skin Cancer / Skin Aging Alert
• Spending time in the sun increases your risk of skin cancer and early skin aging. This product has been shown only to help prevent sunburn, not skin cancer or early skin aging.

• Do not use on damaged or broken skin.

When using this product • keep out of eyes. Rinse with water to remove.

Stop use and ask a doctor if • rash occurs.

Keep out of reach of children.

Directions

• Apply generously 15 minutes before the sun exposure • Children under 6 months of age: ask a doctor. • Reapply at least every 2 hours. • Use a water resistant sunscreen if swimming or sweating Sun Protection Measures: Spending time in the sun increases your risk of skin cancer and early skin aging. To decrease this risk, regularly use a sunscreen with a Broad Spectrum SPF value of 15 or higher and other sun protection measures including: • limit time in the sun, especially from 10 a.m. - 2 p.m. • wear long-sleeved shirts, pants, hats and sunglasses.

Other information

• Protect the product in this container from excessive heat and direct sunlight.

• Store at room temperature: 15C - 30C

Inactive ingredients

Aqua/Water/Eau, Cyclopentasiloxane, Isohexadecane, Ethylhexyl Palmitate, Cetyl PEG/PPG-10/1 Dimethicone, Trimethylsiloxysilicate, Pentylene Glycol, Disteardimonium Hectorite, Adipic Acid, Caprylic Acid, Benzyl PCA, Glycerin, Stearic Acid, Aluminum Hydroxide, Methicone, Sodium Levulinate, PPG-15 Stearyl Ether, Sodium Anisate, Vitis Vinifera (Grape) Seed Oil, Disodium EDTA, Tocopherol, Retinyl Palmitate, Talc, Helianthus Annuus (Sunflower) Seed Oil, Steareth-20, N-Hydroxysuccinimide, BHT, Palmitoyl Tripeptide-1, Chrysin, Palmitoyl Tetrapeptide-7, Chlorhexidine Digluconate, Potassium Sorbate. May Contain (+/-) Iron Oxides (CI 77491, CI 77492, CI 77499)

SILKY SMOOTHING FORMULA VELVETY TOUCH & BRIGHTENING EFFECT

LIQUID FOUNDATION
Evens out the skin tone and provides a velvety appearance through its light formula. Protects the skin against negative external factors thanks to the grape seed oil in its content. Easy application and light texture provides a smooth appearance. Protects the skin from the harmful effects of the sun with SPF 35. Use: Apply a sufficient amount of product on the dry and clean skin in a circular motion with the help of a brush or sponge.

ALIX AVIEN PARIS

34 Rue du l'Escouvrier 95200
Sarcelles PARIS / FRANCE

ALIX AVIEN KOZMETİK San. Tic. A.Ş.

Gazitepe Mah. Aybar Sk. No:7
ISTANBUL / TURKEY

www.celesty.com

Distributed by CELESTY LLC
3970 NW 167TH ST. MIAMI GARDENS,
FL 33054 - USA
info@celesty.com

MADE IN ITALY